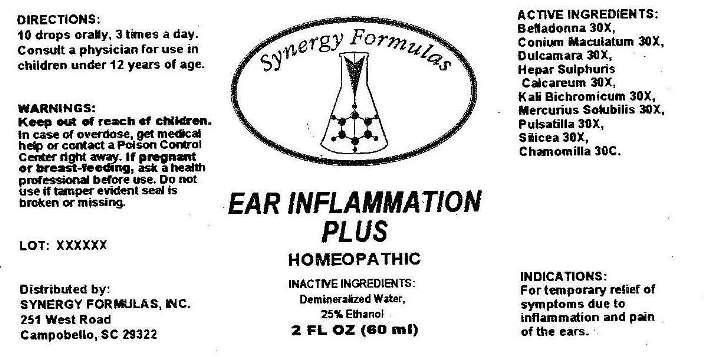 DRUG LABEL: Ear Inflammation Plus
NDC: 43772-0032 | Form: LIQUID
Manufacturer: Synergy Formulas, Inc.
Category: homeopathic | Type: HUMAN OTC DRUG LABEL
Date: 20140513

ACTIVE INGREDIENTS: ATROPA BELLADONNA 30 [hp_X]/1 mL; CONIUM MACULATUM FLOWERING TOP 30 [hp_X]/1 mL; SOLANUM DULCAMARA TOP 30 [hp_X]/1 mL; CALCIUM SULFIDE 30 [hp_X]/1 mL; POTASSIUM DICHROMATE 30 [hp_X]/1 mL; MERCURIUS SOLUBILIS 30 [hp_X]/1 mL; PULSATILLA VULGARIS 30 [hp_X]/1 mL; SILICON DIOXIDE 30 [hp_X]/1 mL; MATRICARIA RECUTITA 30 [hp_C]/1 mL
INACTIVE INGREDIENTS: WATER; ALCOHOL

Drug Facts

ACTIVE INGREDIENTS:

Belladonna 30X, Conium maculatum 30X, Dulcamara 30X, Hepar sulphuris calcareum 30X, Kali bichromicum 30X, Mercurius solubilis 30X, Pulsatilla (Vulgaris) 30X, Silicea 30X, Chamomilla 30C.

INDICAITONS:

For temporary relief of symptoms due to inflammation and pain of the ears.

WARNINGS:

Keep out of the reach of children. In case of overdose, get medical help or contact a Poison Control Center right away.

If pregnant or breast-feeding, ask a health professional before use.

Do not use if tamper evident seal is broken or missing.

Keep out of reach of children. In case of overdose, get medical help or contact a Poison Control Center right away.

DIRECTIONS:

10 drops orally, 3 times a day. Consult a physician for use in children under 12 years of age.

INDICATIONS:

For temporary relief of symptoms due to inflammation and pain of the ears.

INACTIVE INGREDIENTS:

Demineralized Water, 25% Ethanol

QUESTIONS:

Distributed by:

SYNERGY FORMULAS, iNC.

251 West Road

Campobello, SC 29322

PACKAGE LABEL DISPLAY:

Synergy Formulas

EAR INFLAMMATION PLUS

HOMEOPATHIC

2 FL OZ (60 ML)